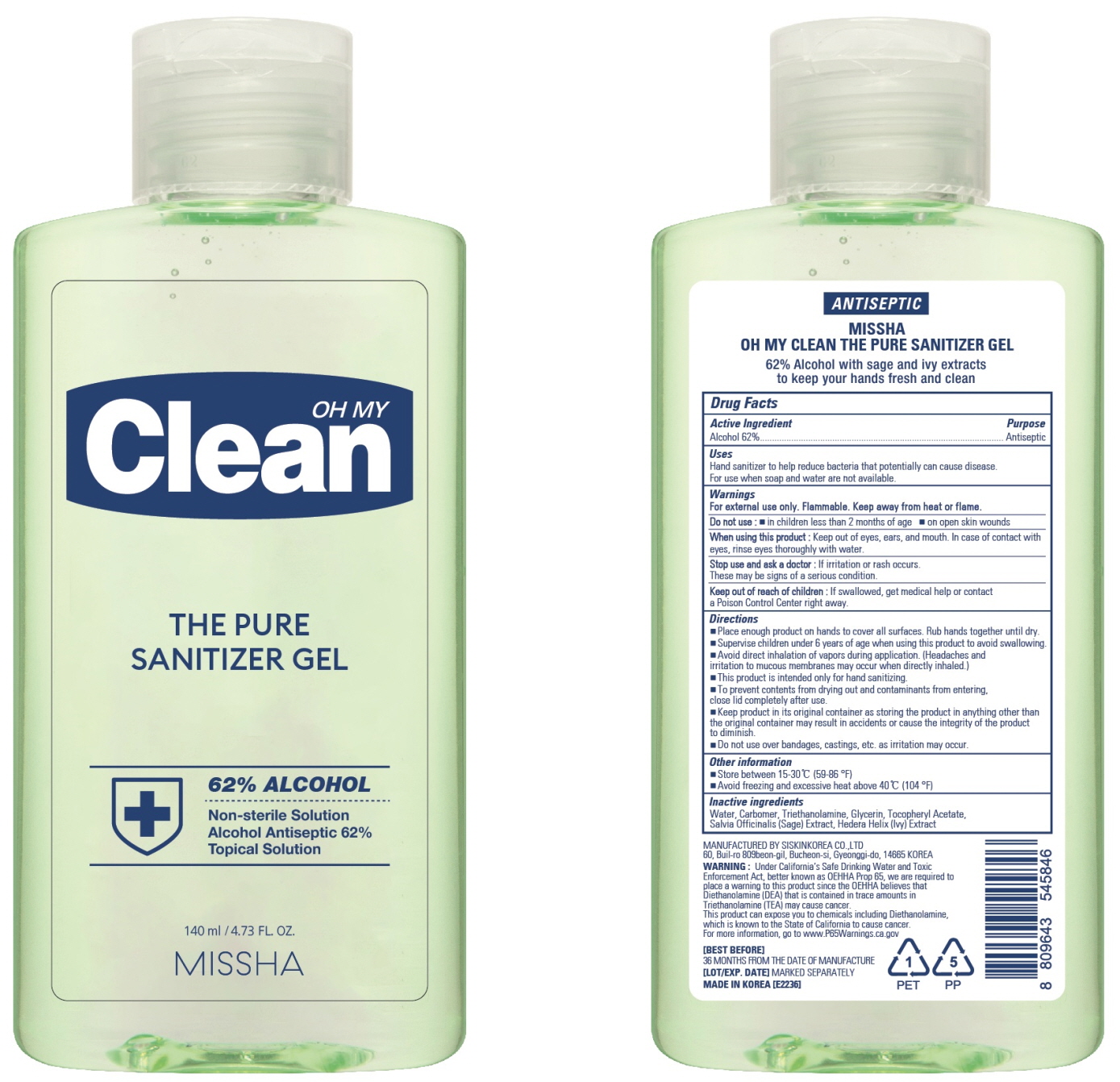 DRUG LABEL: MISSHA OH MY CLEAN THE PURE SANITIZER
NDC: 13733-451 | Form: GEL
Manufacturer: Able C&C Co., Ltd.
Category: otc | Type: HUMAN OTC DRUG LABEL
Date: 20200525

ACTIVE INGREDIENTS: ALCOHOL 86.8 mL/140 mL
INACTIVE INGREDIENTS: Water; CARBOMER HOMOPOLYMER, UNSPECIFIED TYPE; TROLAMINE; Glycerin; .ALPHA.-TOCOPHEROL ACETATE; SALVIA OFFICINALIS ROOT; HEDERA HELIX LEAF

ACTIVE INGREDIENT

Alcohol 62%

INACTIVE INGREDIENT

Water, Carbomer, Triethanolamine, Glycerin, Tocopheryl Acetate, Salvia Officinalis (Sage) Extract, Hedera Helix (Ivy) Extract

PURPOSE

Antiseptic

WARNINGS

For external use only. Flammable. Keep away from heat or flame.

Do not use
■ in children less than 2 months of age ■ on open skin wounds

When using this product
Keep out of eyes, ears, and mouth. In case of contact with eyes, rinse eyes thoroughly with water.

Stop use and ask a doctor
If irritation or rash occurs. These may be signs of a serious condition.

KEEP OUT OF REACH OF CHILDREN

If swallowed, get medical help or contact a Poison Control Center right away.

Uses

Hand sanitizer to help reduce bacteria that potentially can cause disease.
For use when soap and water are not available.

Directions

■ Place enough product on hands to cover all surfaces. Rub hands together until dry.
■Supervise children under 6 years of age when using this product to avoid swallowing.
■ Avoid direct inhalation of vapors during application. (Headaches and irritation to mucous membranes may occur when directly inhaled.)
■ This product is intended only for hand sanitizing.
■ To prevent contents from drying out and contaminants from entering, close lid completely after use.
■ Keep product in its original container as storing the product in anything other than the original container may result in accidents or cause the integrity of the product to diminish.
■ Do not use over bandages, castings, etc. as irritation may occur.

Other information

■ Store between 15-30 ℃ (59-86 °F)
■ Avoid freezing and excessive heat above 40 ℃ (104 °F)